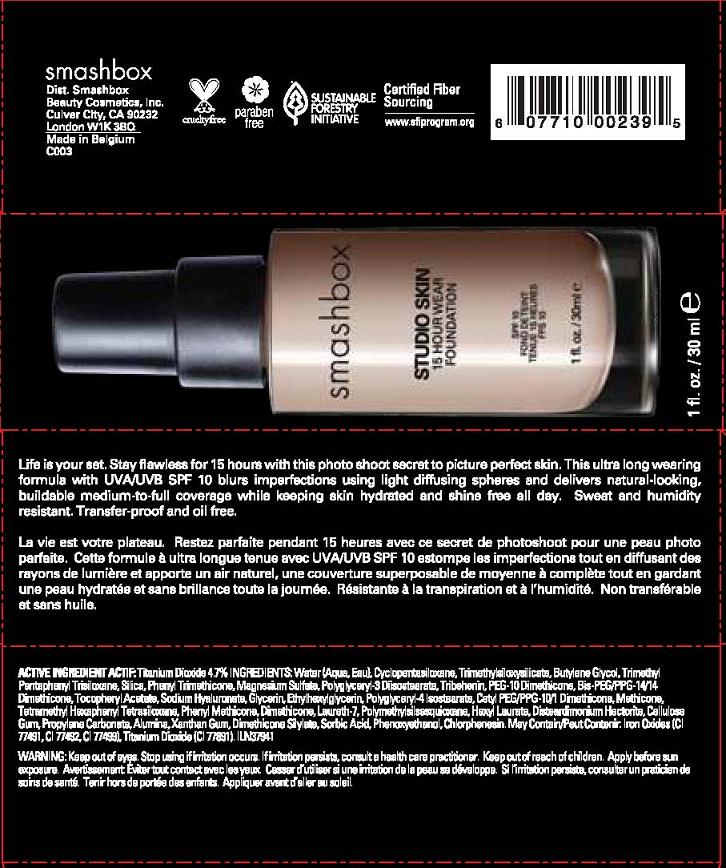 DRUG LABEL: STUDIO SKIN
NDC: 10348-001 | Form: LIQUID
Manufacturer: SMASHBOX  BEAUTY COSMETICS, INC
Category: otc | Type: HUMAN OTC DRUG LABEL
Date: 20110629

ACTIVE INGREDIENTS: TITANIUM DIOXIDE 4.7 mL/100 mL
INACTIVE INGREDIENTS: WATER; CYCLOMETHICONE 5; TRIMETHOXYCAPRYLYLSILANE; BUTYLENE GLYCOL; SILICON DIOXIDE; PHENYL TRIMETHICONE; MAGNESIUM SULFATE, UNSPECIFIED; TRIBEHENIN; ALPHA-TOCOPHEROL ACETATE; HYALURONATE SODIUM; GLYCERIN; ETHYLHEXYLGLYCERIN; POLYGLYCERYL-4 ISOSTEARATE; DIMETHICONE; LAURETH-7; POLYMETHYLSILSESQUIOXANE (11 MICRONS); HEXYL LAURATE; CARBOXYMETHYLCELLULOSE SODIUM; PROPYLENE CARBONATE; ALUMINUM OXIDE; XANTHAN GUM; SORBIC ACID; PHENOXYETHANOL; CHLORPHENESIN; FERROSOFERRIC OXIDE; FERRIC OXIDE RED; FERRIC OXIDE YELLOW

ACTIVE INGREDIENT: TITANIUM DIOXIDE, 4.7%

INACTIVE INGREDIENT

INACTIVE INGREDIENTS: WATER [] CYCLOPENTASILOXANE [] TRIMETHYLSILOXYSILICATE [] BUTYLENE GLYCOL [] TRIMETHYL PENTAPHENYL TRISILOXANE [] SILICA [] PHENYL TRIMETHICONE [] MAGNESIUM SULFATE [] POLYGLYCERYL-3 DIISOSTEARATE [] TRIBEHENIN [] PEG-10 DIMETHICONE [] BIS-PEG/PPG-14/14 DIMETHICONE [] TOCOPHERYL ACETATE [] SODIUM HYALURONATE [] GLYCERIN [] ETHYLHEXYLGLYCERIN [] POLYGLYCERYL-4 ISOSTEARATE [] CETYL PEG/PPG-10/1 DIMETHICONE [] METHICONE [] TETRAMETHYL HEXAPHENYL TETRASILOXANE [] PHENYL METHICONE [] DIMETHICONE [] LAURETH-7 [] POLYMETHYLSILSESQUIOXANE [] HEXYL LAURATE [] DISTEARDIMONIUM HECTORITE [] CELLULOSE GUM [] PROPYLENE CARBONATE [] ALUMINA [] XANTHAN GUM [] DIMETHICONE SILYLATE [] SORBIC ACID [] PHENOXYETHANOL [] CHLORPHENESIN [] [+/- IRON OXIDES (CI 77491, CI 77492, CI 77499) [] TITANIUM DIOXIDE (CI 77891)]

WHEN USING

DIRECTIONS: APPLY BEFORE SUN EXPOSURE.

WARNINGS

WARNING: KEEP OUT OF EYES. STOP USE IF IRRITATION OCCURS. IF IRRITATION PERSISTS, CONSULT A HEALTH PRACTITIONER. KEEP OUT OF REACH OF CHILDREN.

PACKAGE LABEL

PRINCIPAL DISPLAY PANEL

SMASHBOX

STUDIO SKIN

15 HOUR WEAR FOUNDATION

SPF 10

NET WT. 1 FL OZ/30 ML

Smashbox Beauty Cosmetics Inc,

Culver City, CA 90232